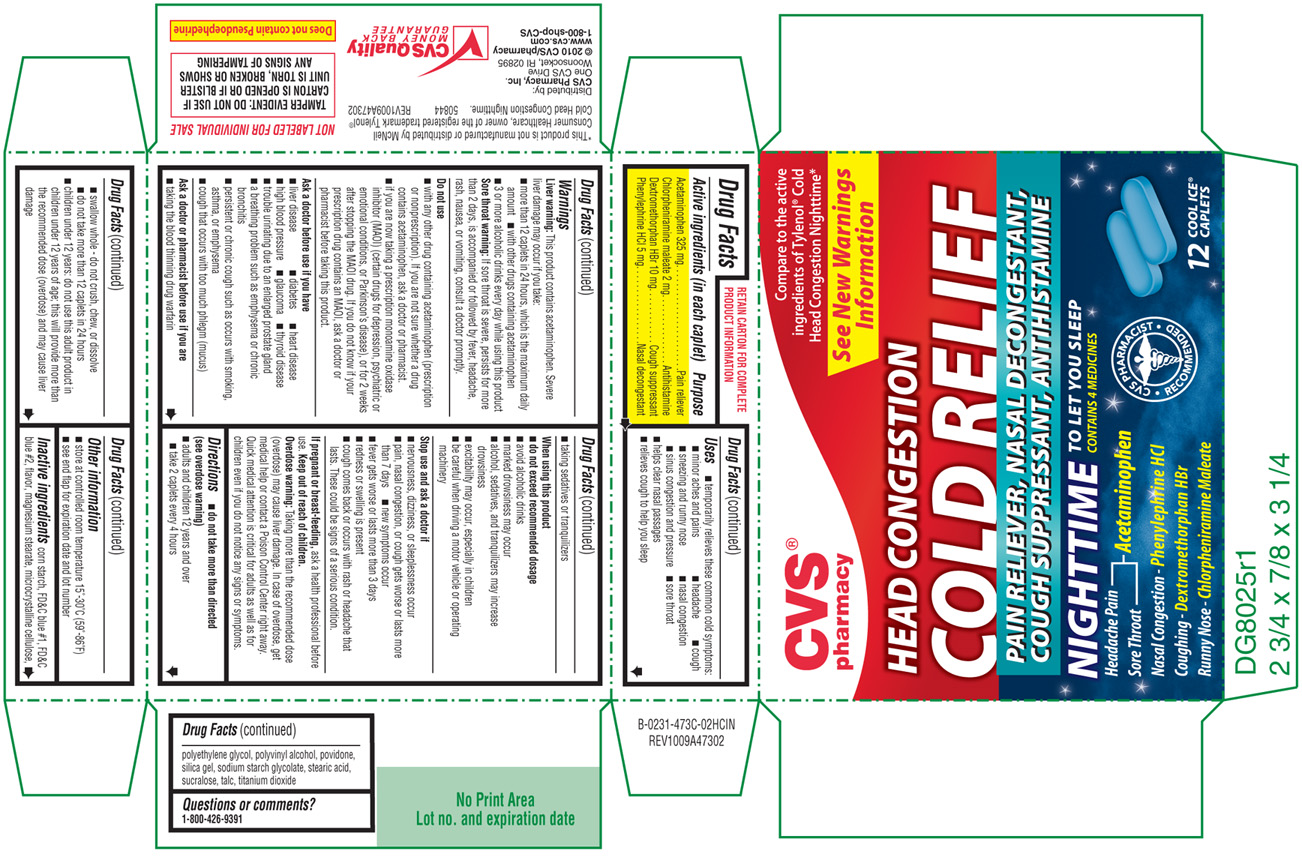 DRUG LABEL: Head Congestion Cold Relief 
NDC: 59779-473 | Form: TABLET, FILM COATED
Manufacturer: WOONSOCKET PRESCRIPTION CENTER, INCORPORATED
Category: otc | Type: HUMAN OTC DRUG LABEL
Date: 20100830

ACTIVE INGREDIENTS: Acetaminophen 325 mg/1 1; Chlorpheniramine Maleate 2 mg/1 1; Dextromethorphan Hydrobromide 10 mg/1 1; Phenylephrine Hydrochloride 5 mg/1 1
INACTIVE INGREDIENTS: Starch, Corn; Fd&c Blue No. 1; Fd&c Blue No. 2; Magnesium Stearate; Cellulose, Microcrystalline; Polyethylene Glycol; Polyvinyl Alcohol; Povidone; Silicon Dioxide; Stearic Acid; Sucralose; Talc; Titanium Dioxide

Active ingredients

(in each caplet)

Acetaminophen 325 mg

Chlorpheniramine maleate 2 mg

Dextromethorphan HBr 10 mg

Phenylephrine HCl 5 mg

Purpose

Pain reliever

Antihistamine

Cough suppressant

Nasal decongestant

Uses

- temporarily relieves these common cold symptoms:
- minor aches and pains
- headache
- cough
- sneezing and runny nose
- nasal congestion
- sinus congestion and pressure
- sore throat
- helps clear nasal passages
- relieves cough to help you sleep

Warnings

Liver warning:

This product contains acetaminophen. Severe liver damage may occur if you take:

- more than 12 caplets in 24 hours, which is the maximum daily amount
- with other drugs containing acetaminophen
- 3 or more alcoholic drinks every day while using this product

Sore throat warning:

If sore throat is severe, persists for more than 2 days, is accompanied or followed by fever, headache, rash, nausea, or vomiting, consult a doctor promptly.

Do not use

- with any other drug containing acetaminophen (prescription or nonprescription). If you are not sure whether a drug contains acetaminophen, ask a doctor or pharmacist.
- if you are now taking a prescription monoamine oxidase inhibitor (MAOI) (certain drugs for depression, psychiatric or emotional conditions, or Parkinson's disease), or for 2 weeks after stopping the MAOI drug, ask a doctor or pharmacist before taking this product.

Ask a doctor before use if you have

- liver disease
- diabetes
- heart disease
- high blood pressure
- glaucoma
- thyroid disease
- trouble urinating due to an enlarged prostate gland
- a breathing problem such as emphysema or chronic bronchitis

Ask a doctor or pharmacist before use if you are

- taking the blood thinning drug warfarin
- taking sedatives or tranquilizers

When using this product

- do not exceed recommended dosage
- avoid alcoholic drinks
- marked drowsiness may occur
- alcohol, sedatives, and tranquilizers may increase drowsiness
- excitability may occur, especially in children
- be careful when driving a motor vehicle or operating machinery

Stop use and ask a doctor if

- nervousness, dizziness, or sleeplessness occur
- pain, nasal congestion, or cough gets worse or lasts more than 7 days
- new symptoms occur
- fever gets worse or lasts more than 3 days
- redness or swelling is present
- cough comes back or occurs with rash or headache that lasts.

These could be signs of a serious condition.

If pregnant or breast-feeding,

ask a health professional before use.

Keep out of reach of children.

Overdose warning: Taking more than the recommended dose (overdose) may cause liver damage. In case of overdose, get medical help or contact a Poison Control Center right away. Quick medical attention is critical for adults as well as for children even if you do not notice any signs or symptoms.

Directions

- do not take more than directed (see overdose warning)
- adults and children 12 years and over
- take 2 caplets every 4 hours
- swallow whole - do not crush, chew, or dissolve
- do not take more than 12 caplets in 24 hours
- children under 12 years: do not use this adult product in children under 12 years of age; this will provide more than the recommended dose (overdose) and may cause liver damage

Other information

- store at controlled room temperature 15°-30°C (59°-86°F)
- see end flap for expiration date and lot number

Inactive ingredients

corn starch, FD&C blue #1, FD&C blue #2, flavor, magnesium stearate, microcrystalline cellulose,polyethylene glycol, polyvinyl alcohol, povidone, silica gel, sodium starch glycolate, stearic acid, sucralose, talc, titanium dioxide

Questions or comments?

1-800-426-9391

PRODUCT PACKAGING

The product packaging shown below represents a sample of that currently in use. Additional packaging may also be available.

CVS®

pharmacy

Compare to the active

ingredients of Tylenol® Cold

Head Congestion Nighttime*

See New Warnings

Information

HEAD CONGESTION

COLD RELIEF

PAIN RELIEVER, NASAL DECONGESTANT,

COUGH SUPPRESSANT, ANTIHISTAMINE

NIGHTTIME

TO LET YOU SLEEP

CONTAINS 4 MEDICINES

Headache Pain -

- Acetaminophen

Sore Throat -

Nasal Congestion - Phenylephrine HCl

Coughing - Dextromethorphan HBr

Runny Nose - Chlorpheniramine Maleate

12 COOL ICE® CAPLETS

TAMPER EVIDENT: DO NOT USE IF CARTON IS OPENED OR IF BLISTER UNIT IS TORN, BROKEN OR SHOWS ANY SIGNS OF TAMPERING

50844 REV1009A47302

Distributed by:

CVS Pharmacy, Inc.

One CVS Drive

Woonsocket, RI 02895

© 2010 CVS/pharmacy

www.cvs.com

1-800-shop-CVS